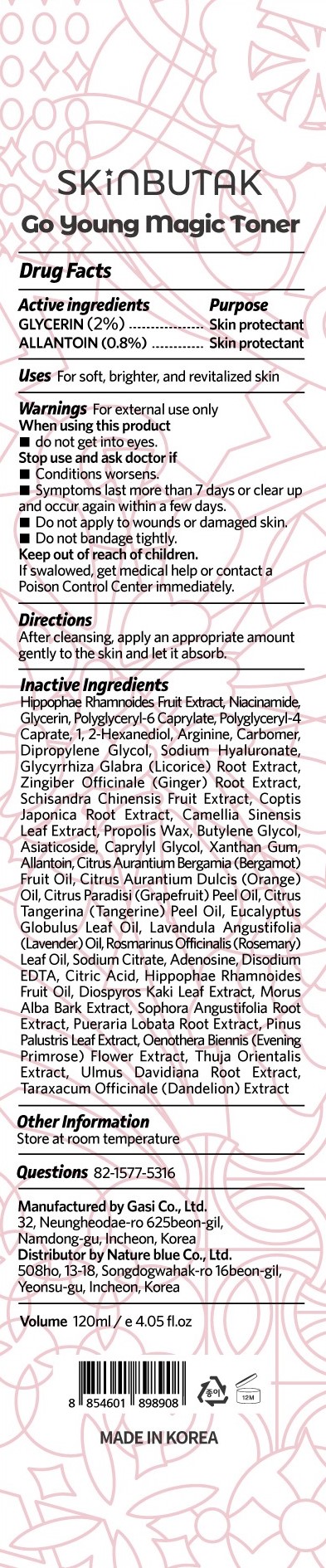 DRUG LABEL: SKINBUTAK GO YOUNG MAGIC TONER
NDC: 81851-203 | Form: LIQUID
Manufacturer: NatureBlue Co.,Ltd
Category: otc | Type: HUMAN OTC DRUG LABEL
Date: 20210428

ACTIVE INGREDIENTS: GLYCERIN 2 mg/100 mL; ALLANTOIN 0.8 mg/100 mL
INACTIVE INGREDIENTS: HIPPOPHAE RHAMNOIDES FRUIT; GLYCYRRHIZA GLABRA; CAPRYLYL GLYCOL; NIACINAMIDE; DIPROPYLENE GLYCOL; SCHISANDRA CHINENSIS FRUIT; EDETATE DISODIUM ANHYDROUS; ARGININE; CARBOMER HOMOPOLYMER, UNSPECIFIED TYPE; COPTIS JAPONICA ROOT; GREEN TEA LEAF; ASIATICOSIDE; ORANGE OIL, COLD PRESSED; GRAPEFRUIT OIL; MANDARIN OIL; ROSEMARY OIL; SODIUM CITRATE, UNSPECIFIED FORM; CITRIC ACID MONOHYDRATE; MORUS ALBA BARK; SOPHORA FLAVESCENS ROOT; PINUS PALUSTRIS LEAF; OENOTHERA BIENNIS FLOWER; POLYGLYCERYL-6 CAPRYLATE; POLYGLYCERYL-4 CAPRATE; 1,2-HEXANEDIOL; HYALURONATE SODIUM; GINGER; PROPOLIS WAX; BUTYLENE GLYCOL; EUCALYPTUS OIL; LAVENDER OIL; ADENOSINE; HIPPOPHAE RHAMNOIDES FRUIT OIL; DIOSPYROS KAKI LEAF; PUERARIA MONTANA VAR. LOBATA ROOT; ULMUS DAVIDIANA ROOT; TARAXACUM OFFICINALE; XANTHAN GUM; BERGAMOT OIL

81851-203 SKINBUTAK GO YOUNG MAGIC TONER

Active ingredients

GLYCERIN (2%)
ALLANTOIN (0.8%)

Purpose

Skin protectant

Uses

For soft, brighter, and revitalized skin

Warnings

For external use only.

If swalowed, get medical help or contact a Poison Control Center immediately.

When using this product

- do not get into eyes.

Stop use and ask doctor if

- Conditions worsens.
- Symptoms last more than 7 days or clear up and occur again within a few days.
- Do not apply to wounds or damaged skin.
- Do not bandage tightly.

Keep out of reach of children

Directions

After cleansing, apply an appropriate amount gently to the skin and let it absorb.

Inactive Ingredients

Hippophae Rhamnoides Fruit Extract, Niacinamide, Glycerin, Polyglyceryl-6 Caprylate, Polyglyceryl-4 Caprate, 1, 2-Hexanediol, Arginine, Carbomer, Dipropylene Glycol, Sodium Hyaluronate, Glycyrrhiza Glabra (Licorice) Root Extract, Zingiber Officinale (Ginger) Root Extract, Schisandra Chinensis Fruit Extract, Coptis Japonica Root Extract, Camellia Sinensis Leaf Extract, Propolis Wax, Butylene Glycol, Asiaticoside, Caprylyl Glycol, Xanthan Gum, Allantoin, Citrus Aurantium Bergamia (Bergamot) Fruit Oil, Citrus Aurantium Dulcis (Orange) Oil, Citrus Paradisi (Grapefruit) Peel Oil, Citrus Tangerina (Tangerine) Peel Oil, Eucalyptus Globulus Leaf Oil, Lavandula Angustifolia (Lavender) Oil, Rosmarinus Officinalis (Rosemary) Leaf Oil, Sodium Citrate, Adenosine, Disodium EDTA, Citric Acid, Hippophae Rhamnoides Fruit Oil, Diospyros Kaki Leaf Extract, Morus Alba Bark Extract, Sophora Angustifolia Root Extract, Pueraria Lobata Root Extract, Pinus Palustris Leaf Extract, Oenothera Biennis (Evening Primrose) Flower Extract, Thuja Orientalis Extract, Ulmus Davidiana Root Extract, Taraxacum Officinale (Dandelion) Extract

Other Information

Store at room temperature